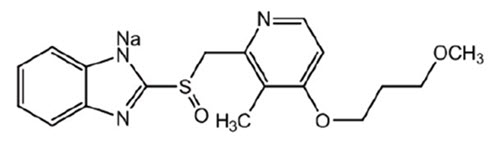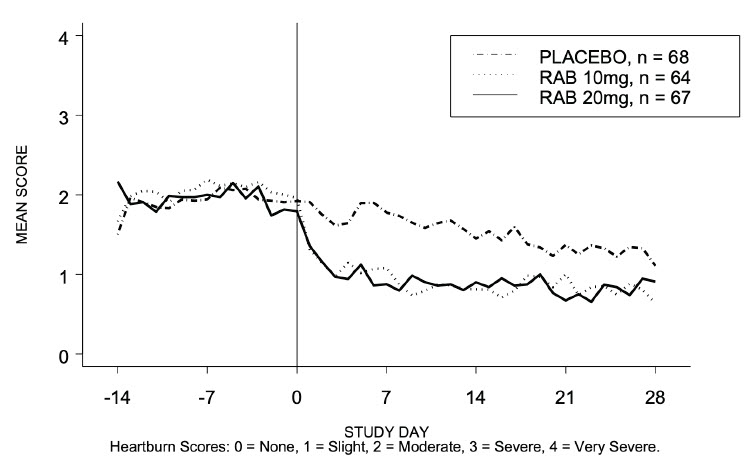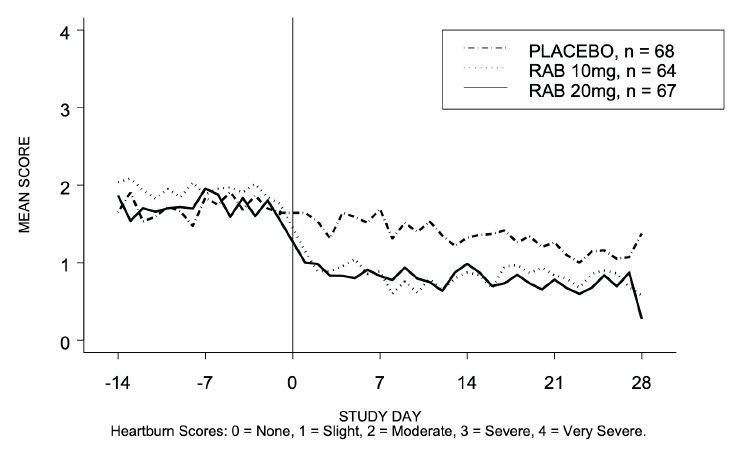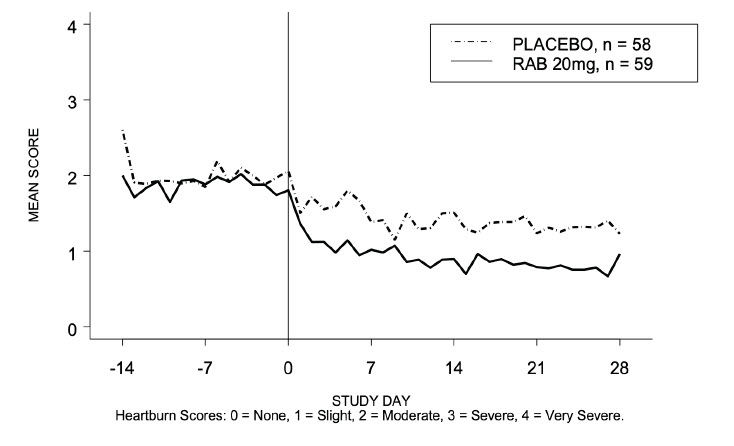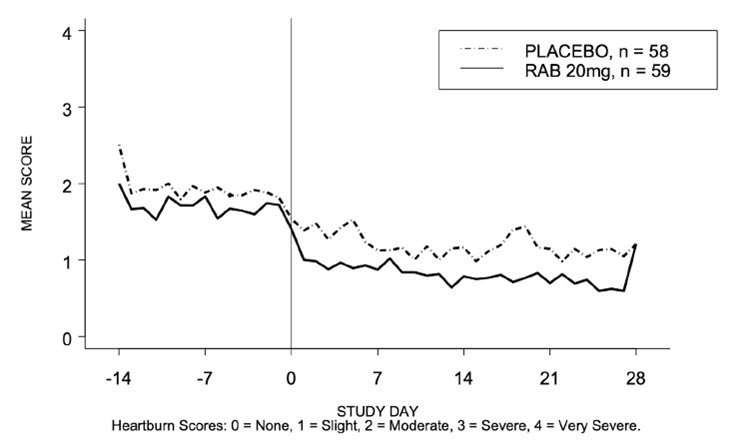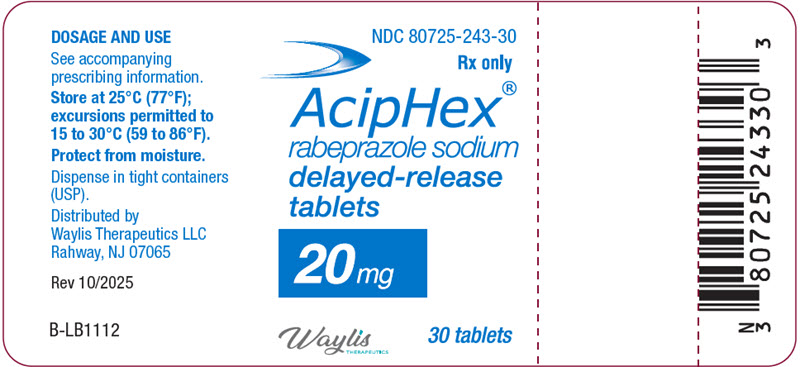 DRUG LABEL: Aciphex
NDC: 80725-243 | Form: TABLET, DELAYED RELEASE
Manufacturer: Waylis Therapeutics LLC
Category: prescription | Type: HUMAN PRESCRIPTION DRUG LABEL
Date: 20260127

ACTIVE INGREDIENTS: rabeprazole sodium 20 mg/1 1
INACTIVE INGREDIENTS: CARNAUBA WAX; CROSPOVIDONE, UNSPECIFIED; DIACETYLATED MONOGLYCERIDES; ETHYLCELLULOSE, UNSPECIFIED; HYDROXYPROPYL CELLULOSE (1600000 WAMW); HYDROXYPROPYL CELLULOSE (90000 WAMW); HYPROMELLOSE PHTHALATE (24% PHTHALATE, 55 CST); MAGNESIUM STEARATE; MANNITOL; SODIUM HYDROXIDE; SODIUM STEARYL FUMARATE; TALC; TITANIUM DIOXIDE; FERRIC OXIDE YELLOW; FERRIC OXIDE RED

HIGHLIGHTS OF PRESCRIBING INFORMATION

These highlights do not include all the information needed to use ACIPHEX DELAYED-RELEASE TABLETS safely and effectively. See full prescribing information for ACIPHEX DELAYED-RELEASE TABLETS.
ACIPHEX® (rabeprazole sodium) delayed-release tablets, for oral use
Initial U.S. Approval: 1999

1 INDICATIONS AND USAGE

ACIPHEX delayed-release tablets is a proton pump inhibitor (PPI) indicated in adults for:

- Healing of Erosive or Ulcerative Gastroesophageal Reflux Disease (GERD) (1.1).
- Maintenance of Healing of Erosive or Ulcerative GERD (1.2).
- Treatment of Symptomatic GERD (1.3).
- Healing of Duodenal Ulcers (1.4).
- Helicobacter pylori Eradication to Reduce Risk of Duodenal Ulcer Recurrence (1.5).
- Treatment of Pathological Hypersecretory Conditions, Including Zollinger-Ellison Syndrome (1.6).

In adolescent patients 12 years of age and older for:

- Short-term Treatment of Symptomatic GERD (1.7).

2 DOSAGE AND ADMINISTRATION

Indication | Recommended Dosage (2)
Healing of Erosive or Ulcerative Gastroesophageal Reflux Disease (GERD) | 20 mg once daily for 4 to 8 weeks
Maintenance of Healing of Erosive or Ulcerative GERD* studied for 12 months | 20 mg once daily*
Symptomatic GERD in Adults | 20 mg once daily for 4 weeks
Healing of Duodenal Ulcers | 20 mg once daily after morning meal for up to 4 weeks
Helicobacter pylori Eradication to Reduce the Risk of Duodenal Ulcer Recurrence Three Drug Regimen: ACIPHEX 20 mg Amoxicillin 1000 mg Clarithromycin 500 mg | All three medications should be taken twice daily with morning and evening meals for 7 days
Pathological Hypersecretory Conditions, Including Zollinger-Ellison Syndrome | Starting dose 60 mg once daily then adjust to patient needs
Symptomatic GERD in Adolescents 12 Years of Age and Older | 20 mg once daily for up to 8 weeks

Administration Instructions (2):

- Swallow ACIPHEX delayed-release tablets whole. Do not chew, crush or split the tablets.
- For the treatment of duodenal ulcers take ACIPHEX delayed-release tablets after a meal.
- For Helicobacter pylori eradication take ACIPHEX delayed-release tablets with food.
- For all other indications ACIPHEX delayed-release tablets can be taken with or without food.

3 DOSAGE FORMS AND STRENGTHS

Delayed-Release Tablets: 20 mg (3).

4 CONTRAINDICATIONS

- Patients with a history of hypersensitivity to rabeprazole (4).
- PPIs, including ACIPHEX delayed-release tablets, are contraindicated in patients receiving rilpivirine-containing products (4, 7).
- Refer to the Contraindications section of the prescribing information for clarithromycin and amoxicillin, when administered in combination with ACIPHEX (4).

5 WARNINGS AND PRECAUTIONS

- Gastric Malignancy: In adults, symptomatic response to therapy with rabeprazole does not preclude the presence of gastric malignancy. Consider additional follow-up and diagnostic testing (5.1).
- Use with Warfarin: Monitor for increases in INR and prothrombin time (5.2, 7).
- Acute Tubulointerstitial Nephritis: Discontinue treatment and evaluate patients (5.3).
- Clostridium difficile-Associated Diarrhea: PPI therapy may be associated with increased risk of (5.4).
- Bone Fracture: Long-term and multiple daily dose PPI therapy may be associated with an increased risk for osteoporosis-related fractures of the hip, wrist, or spine (5.5).
- Severe Cutaneous Adverse Reactions: Discontinue at the first signs or symptoms of severe cutatneous adverse reactions or other signs of hypersensitivity and consider further evaluation (5.6).
- Cutaneous and Systemic Lupus Erythematosus: Mostly cutaneous, new onset or exacerbation of existing disease; discontinue ACIPHEX and refer to specialist for evaluation (5.7).
- Cyanocobalamin (Vitamin B-12) Deficiency: Daily long-term use (e.g., longer than 3 years) may lead to malabsorption or a deficiency of cyanocobalamin (5.8).
- Hypomagnesemia and Mineral Metabolism: Reported rarely with prolonged treatment with PPIs (5.9).
- Interaction with Methotrexate: Concomitant use with PPIs may elevate and/or prolong serum concentrations of methotrexate and/or its metabolite, possibly leading to toxicity. With high dose methotrexate administration, consider a temporary withdrawal of ACIPHEX delayed-release tablets (5.10, 7).
- Fundic Gland Polyps: Risk increases with long-term use, especially beyond one year. Use the shortest duration of therapy (5.11).

6 ADVERSE REACTIONS

- Most common adverse reactions in adults (>2%) are pain, pharyngitis, flatulence, infection, and constipation (6.1).
- Most common adverse reactions in adolescents (≥2%) are headache, diarrhea, nausea, vomiting, and abdominal pain (6.1).

To report SUSPECTED ADVERSE REACTIONS, contact Waylis Therapeutics LLC at 1-844-944-0912 or FDA at 1-800-FDA-1088 or www.fda.gov/medwatch

7 DRUG INTERACTIONS

See full prescribing information for a list of clinically important drug interactions (7).

8 USE IN SPECIFIC POPULATIONS

Pediatric Use: Dosage strength not appropriate for patients less than 12 years (2, 8.4).

FULL PRESCRIBING INFORMATION

1 INDICATIONS AND USAGE

1.1 Healing of Erosive or Ulcerative GERD in Adults

ACIPHEX delayed-release tablets are indicated for short-term (4 to 8 weeks) treatment in the healing and symptomatic relief of erosive or ulcerative gastroesophageal reflux disease (GERD). For those patients who have not healed after 8 weeks of treatment, an additional 8-week course of ACIPHEX may be considered.

1.2 Maintenance of Healing of Erosive or Ulcerative GERD in Adults

ACIPHEX delayed-release tablets are indicated for maintaining healing and reduction in relapse rates of heartburn symptoms in patients with erosive or ulcerative gastroesophageal reflux disease (GERD Maintenance). Controlled studies do not extend beyond 12 months.

1.3 Treatment of Symptomatic GERD in Adults

ACIPHEX delayed-release tablets are indicated for the treatment of daytime and nighttime heartburn and other symptoms associated with GERD in adults for up to 4 weeks.

1.4 Healing of Duodenal Ulcers in Adults

ACIPHEX delayed-release tablets are indicated for short-term (up to four weeks) treatment in the healing and symptomatic relief of duodenal ulcers. Most patients heal within four weeks.

1.5 Helicobacter pylori Eradication to Reduce the Risk of Duodenal Ulcer Recurrence in Adults

ACIPHEX delayed-release tablets, in combination with amoxicillin and clarithromycin as a three drug regimen, are indicated for the treatment of patients with H. pylori infection and duodenal ulcer disease (active or history within the past 5 years) to eradicate H. pylori. Eradication of H. pylori has been shown to reduce the risk of duodenal ulcer recurrence.

In patients who fail therapy, susceptibility testing should be done. If resistance to clarithromycin is demonstrated or susceptibility testing is not possible, alternative antimicrobial therapy should be instituted [see Clinical Pharmacology (12.2) and the full prescribing information for clarithromycin].

1.6 Treatment of Pathological Hypersecretory Conditions, Including Zollinger-Ellison Syndrome in Adults

ACIPHEX delayed-release tablets are indicated for the long-term treatment of pathological hypersecretory conditions, including Zollinger-Ellison syndrome.

1.7 Treatment of Symptomatic GERD in Adolescent Patients 12 Years of Age and Older

ACIPHEX delayed-release tablets are indicated for the treatment of symptomatic GERD in adolescents 12 years of age and above for up to 8 weeks.

2 DOSAGE AND ADMINISTRATION

Table 1 shows the recommended dosage of ACIPHEX delayed-release tablets in adults and adolescent patients 12 years of age and older. The use of ACIPHEX delayed-release tablets is not recommended for use in pediatric patients 1 year to less than 12 years of age because the lowest available tablet strength (20 mg) exceeds the recommended dose for these patients. Use another rabeprazole formulation for pediatric patients 1 year to less than 12 years of age.

Table 1: Recommended Dosage and Duration of ACIPHEX Delayed-Release Tablets in Adults and Adolescents 12 Years of Age and Older
Indication | Dosage of ACIPHEX delayed-release tablets | Treatment Duration
Adults
Healing of Erosive or Ulcerative Gastroesophageal Reflux Disease (GERD) | 20 mg once daily | 4 to 8 weeks [For those patients who have not healed after 8 weeks of treatment, an additional 8-week course of ACIPHEX may be considered.]
Maintenance of Healing of Erosive or Ulcerative GERD | 20 mg once daily | Controlled studies do not extend beyond 12 months
Symptomatic GERD in Adults | 20 mg once daily | Up to 4 weeks [If symptoms do not resolve completely after 4 weeks, an additional course of treatment may be considered.]
Healing of Duodenal Ulcers | 20 mg once daily after the morning meal | Up to 4 weeks [Most patients heal within 4 weeks; some patients may require additional therapy to achieve healing.]
Helicobacter pylori Eradication to Reduce the Risk of Duodenal Ulcer Recurrence | ACIPHEX 20 mg Amoxicillin 1000 mg Clarithromycin 500 mg Take all three medications twice daily with morning and evening meals; it is important that patients comply with the full 7-day regimen [see Clinical Studies (14.5)] | 7 days
Pathological Hypersecretory Conditions, Including Zollinger-Ellison Syndrome | Starting dose 60 mg once daily then adjust to patient needs; some patients require divided doses Dosages of 100 mg once daily and 60 mg twice daily have been administered | As long as clinically indicated Some patients with Zollinger-Ellison syndrome have been treated continuously for up to one year
Adolescents 12 Years of Age and Older
Symptomatic GERD | 20 mg once daily | Up to 8 weeks

Administration Instructions

- Swallow ACIPHEX delayed-release tablets whole. Do not chew, crush, or split tablets.
- For the treatment of duodenal ulcers take ACIPHEX delayed-release tablets after a meal.
- For Helicobacter pylori eradication take ACIPHEX delayed-release tablets with food.
- For all other indications ACIPHEX delayed-release tablets can be taken with or without food.
- Take a missed dose as soon as possible. If it is almost time for the next dose, skip the missed dose and go back to the normal schedule. Do not take two doses at the same time.

3 DOSAGE FORMS AND STRENGTHS

ACIPHEX delayed-release tablets are provided in one strength, 20 mg. The tablets are round, light yellow, enteric coated, biconvex tablets. "ACIPHEX 20" is imprinted in red on one side of the tablet.

4 CONTRAINDICATIONS

- ACIPHEX is contraindicated in patients with known hypersensitivity to rabeprazole, substituted benzimidazoles, or to any component of the formulation. Hypersensitivity reactions may include anaphylaxis, anaphylactic shock, angioedema, bronchospasm, acute tubulointerstitial nephritis, and urticaria [see Warnings and Precautions (5.3), Adverse Reactions (6)].
- PPIs, including ACIPHEX, are contraindicated with rilpivirine-containing products [see Drug Interactions (7)].
- For information about contraindications of antibacterial agents (clarithromycin and amoxicillin) indicated in combination with ACIPHEX delayed-release tablets, refer to the Contraindications section of their package inserts.

5 WARNINGS AND PRECAUTIONS

5.1 Presence of Gastric Malignancy

In adults, symptomatic response to therapy with ACIPHEX does not preclude the presence of gastric malignancy. Consider additional follow-up and diagnostic testing in adult patients who have a suboptimal response or an early symptomatic relapse after completing treatment with a PPI.

5.2 Interaction with Warfarin

Steady state interactions of rabeprazole and warfarin have not been adequately evaluated in patients. There have been reports of increased INR and prothrombin time in patients receiving a proton pump inhibitor and warfarin concomitantly. Increases in INR and prothrombin time may lead to abnormal bleeding and even death. Patients treated with ACIPHEX delayed-release tablets and warfarin concomitantly may need to be monitored for increases in INR and prothrombin time [see Drug Interactions (7)].

5.3 Acute Tubulointerstitial Nephritis

Acute tubulointerstitial nephritis (TIN) has been observed in patients taking PPIs and may occur at any point during PPI therapy. Patients may present with varying signs and symptoms from symptomatic hypersensitivity reactions, to non-specific symptoms of decreased renal function (e.g., malaise, nausea, anorexia). In reported case series, some patients were diagnosed on biopsy and in the absence of extra-renal manifestations (e.g., fever, rash or arthralgia).

Discontinue ACIPHEX and evaluate patients with suspected acute TIN [see Contraindication (4)].

5.4 Clostridium difficile-Associated Diarrhea

Published observational studies suggest that PPI therapy like ACIPHEX may be associated with an increased risk of Clostridium difficile-associated diarrhea, especially in hospitalized patients. This diagnosis should be considered for diarrhea that does not improve [see Adverse Reactions (6.2)].

Patients should use the lowest dose and shortest duration of PPI therapy appropriate to the condition being treated.

Clostridium difficile-associated diarrhea (CDAD) has been reported with use of nearly all antibacterial agents. For more information specific to antibacterial agents (clarithromycin and amoxicillin) indicated for use in combination with ACIPHEX, refer to Warnings and Precautions sections of the corresponding prescribing information.

5.5 Bone Fracture

Several published observational studies in adults suggest that PPI therapy may be associated with an increased risk for osteoporosis-related fractures of the hip, wrist, or spine. The risk of fracture was increased in patients who received high-dose, defined as multiple daily doses, and long-term PPI therapy (a year or longer). Patients should use the lowest dose and shortest duration of PPI therapy appropriate to the condition being treated. Patients at risk for osteoporosis-related fractures should be managed according to established treatment guidelines [see Dosage and Administration (2), Adverse Reactions (6.2)].

5.6 Severe Cutaneous Adverse Reactions

Severe cutaneous adverse reactions, including Stevens-Johnson syndrome (SJS) and toxic epidermal necrolysis (TEN), drug reaction with eosinophilia and systemic symptoms (DRESS), and acute generalized exanthematous pustulosis (AGEP) have been reported in association with the use of PPIs [see Adverse Reactions (6.2)]. Discontinue ACIPHEX at first signs or symptoms of severe cutaneous adverse reactions or other signs of hypersensitivity and consider further evaluation.

5.7 Cutaneous and Systemic Lupus Erythematosus

Cutaneous lupus erythematosus (CLE) and systemic lupus erythematosus (SLE) have been reported in patients taking PPIs, including rabeprazole. These events have occurred as both new onset and an exacerbation of existing autoimmune disease. The majority of PPI-induced lupus erythematosus cases were CLE.

The most common form of CLE reported in patients treated with PPIs was subacute CLE (SCLE) and occurred within weeks to years after continuous drug therapy in patients ranging from infants to the elderly. Generally, histological findings were observed without organ involvement.

Systemic lupus erythematosus (SLE) is less commonly reported than CLE in patients receiving PPIs. PPI associated SLE is usually milder than non-drug induced SLE. Onset of SLE typically occurred within days to years after initiating treatment primarily in patients ranging from young adults to the elderly. The majority of patients presented with rash; however, arthralgia and cytopenia were also reported.

Avoid administration of PPIs for longer than medically indicated. If signs or symptoms consistent with CLE or SLE are noted in patients receiving ACIPHEX, discontinue the drug and refer the patient to the appropriate specialist for evaluation. Most patients improve with discontinuation of the PPI alone in 4 to 12 weeks. Serological testing (e.g. ANA) may be positive and elevated serological test results may take longer to resolve than clinical manifestations.

5.8 Cyanocobalamin (Vitamin B-12) Deficiency

Daily treatment with any acid-suppressing medications over a long period of time (e.g., longer than 3 years) may lead to malabsorption of cyanocobalamin (vitamin B-12) caused by hypo- or achlorhydria. Rare reports of cyanocobalamin deficiency occurring with acid-suppressing therapy have been reported in the literature. This diagnosis should be considered if clinical symptoms consistent with cyanocobalamin deficiency are observed in patients treated with ACIPHEX.

5.9 Hypomagnesemia and Mineral Metabolism

Hypomagnesemia, symptomatic and asymptomatic, has been reported rarely in patients treated with PPIs for at least three months, in most cases after a year of therapy. Serious adverse events include tetany, arrhythmias, and seizures. Hypomagnesemia may lead to hypocalcemia and/or hypokalemia and may exacerbate underlying hypocalcemia in at-risk patients. In most patients, treatment of hypomagnesemia required magnesium replacement and discontinuation of the PPI.

For patients expected to be on prolonged treatment or who take PPIs with medications such as digoxin or drugs that may cause hypomagnesemia (e.g., diuretics), health care professionals may consider monitoring magnesium levels prior to initiation of PPI treatment and periodically [see Adverse Reactions (6.2)].

Consider monitoring magnesium and calcium levels prior to initiation of ACIPHEX and periodically while on treatment in patients with a preexisting risk of hypocalcemia (e.g., hypoparathyroidism). Supplement with magnesium and/or calcium as necessary. If hypocalcemia is refractory to treatment, consider discontinuing the PPI.

5.10 Interaction with Methotrexate

Literature suggests that concomitant use of PPIs with methotrexate (primarily at high dose; see methotrexate prescribing information) may elevate and prolong serum concentrations of methotrexate and/or its metabolite, possibly leading to methotrexate toxicities. In high-dose methotrexate administration, a temporary withdrawal of the PPI may be considered in some patients [see Drug Interactions (7)].

5.11 Fundic Gland Polyps

PPI use is associated with an increased risk of fundic gland polyps that increases with long-term use, especially beyond one year. Most PPI users who developed fundic gland polyps were asymptomatic and fundic gland polyps were identified incidentally on endoscopy. Use the shortest duration of PPI therapy appropriate to the condition being treated.

6 ADVERSE REACTIONS

The following serious adverse reactions are described below and elsewhere in labeling:

- Acute Tubulointerstitial Nephritis [see Warnings and Precautions (5.3)]
- Clostridium difficile-Associated Diarrhea [see Warnings and Precautions (5.4)]
- Bone Fracture [see Warnings and Precautions (5.5)]
- Cutaneous and Systemic Lupus Erythematosus [see Warnings and Precautions (5.7)]
- Cyanocobalamin (Vitamin B-12) Deficiency [see Warnings and Precautions (5.8)]
- Hypomagnesemia and Mineral Metabolism [see Warnings and Precautions (5.9)]
- Fundic Gland Polyps [see Warnings and Precautions (5.11)]

6.1 Clinical Studies Experience

Because clinical trials are conducted under varying conditions, adverse reaction rates observed in the clinical trials of a drug cannot be directly compared to rates in the clinical trials of another drug and may not reflect the rates observed in practice.

Adults

The data described below reflect exposure to ACIPHEX delayed-release tablets in 1064 adult patients exposed for up to 8 weeks. The studies were primarily placebo- and active-controlled trials in adult patients with Erosive or Ulcerative Gastroesophageal Reflux Disease (GERD), Duodenal Ulcers and Gastric Ulcers. The population had a mean age of 53 years (range 18-89 years) and had a ratio of approximately 60% male: 40% female. The racial distribution was 86% Caucasian, 8% African American, 2% Asian, and 5% other. Most patients received either 10 mg, 20 mg or 40 mg per day of ACIPHEX delayed-release tablets.

An analysis of adverse reactions appearing in ≥2% of patients treated with ACIPHEX delayed-release tablets (n=1064) and with a greater frequency than placebo (n=89) in controlled North American and European acute treatment trials, revealed the following adverse reactions: pain (3% vs. 1%), pharyngitis (3% vs. 2%), flatulence (3% vs. 1%), infection (2% vs. 1%), and constipation (2% vs. 1%).

Three long-term maintenance studies consisted of a total of 740 adult patients; at least 54% of adult patients were exposed to ACIPHEX delayed-release tablets for 6 months and at least 33% were exposed for 12 months. Of the 740 adult patients, 247 (33%) and 241 (33%) patients received 10 mg and 20 mg of ACIPHEX delayed-release tablets, respectively, while 169 (23%) patients received placebo and 83 (11%) received omeprazole.

The safety profile of rabeprazole in the maintenance studies in adults was consistent with what was observed in the acute studies.

Less common adverse reactions seen in controlled clinical trials (<2% of patients treated with ACIPHEX delayed-release tablets and greater than placebo) and for which there is a possibility of a causal relationship to rabeprazole, include the following: headache, abdominal pain, diarrhea, dry mouth, dizziness, peripheral edema, hepatic enzyme increase, hepatitis, hepatic encephalopathy, myalgia, and arthralgia.

Combination Treatment with Amoxicillin and Clarithromycin: In clinical trials using combination therapy with rabeprazole plus amoxicillin and clarithromycin (RAC), no adverse reactions unique to this drug combination were observed. In the U.S. multicenter study, the most frequently reported drug related adverse reactions for patients who received RAC therapy for 7 or 10 days were diarrhea (8% and 7%) and taste perversion (6% and 10%), respectively.

No clinically significant laboratory abnormalities particular to the drug combinations were observed.

For more information on adverse reactions or laboratory changes with amoxicillin or clarithromycin, refer to their respective prescribing information, Adverse Reactions section.

Pediatrics

In a multicenter, open-label study of adolescent patients 12 to 16 years of age with a clinical diagnosis of symptomatic GERD or endoscopically proven GERD, the adverse event profile was similar to that of adults. The adverse reactions reported without regard to relationship to ACIPHEX delayed-release tablets that occurred in ≥2% of 111 patients were headache (9.9%), diarrhea (4.5%), nausea (4.5%), vomiting (3.6%), and abdominal pain (3.6%). The related reported adverse reactions that occurred in ≥2% of patients were headache (5.4%) and nausea (1.8%). There were no adverse reactions reported in this study that were not previously observed in adults.

6.2 Postmarketing Experience

The following adverse reactions have been identified during post approval use of rabeprazole. Because these reactions are reported voluntarily from a population of uncertain size, it is not always possible to reliably estimate their frequency or establish a causal relationship to drug exposure:

Blood and Lymphatic System Disorders: agranulocytosis, hemolytic anemia, leukopenia, pancytopenia, thrombocytopenia

Ear and Labyrinth Disorders: vertigo

Eye Disorders: blurred vision

Gastrointestinal Disorders: fundic gland polyps

General Disorders and Administration Site Conditions: sudden death

Hepatobiliary Disorders: jaundice

Immune System Disorders: anaphylaxis, angioedema, systemic lupus erythematosus, Stevens-Johnson syndrome, toxic epidermal necrolysis (some fatal), DRESS, AGEP

Infections and Infestations: Clostridium difficile-associated diarrhea

Investigations: Increases in prothrombin time/INR (in patients treated with concomitant warfarin), TSH elevations

Metabolism and Nutrition Disorders: hyperammonemia, hypomagnesemia, hypocalcemia, hypokalemia [Warnings and Precautions 5.8], hyponatremia

Musculoskeletal System Disorders: bone fracture, rhabdomyolysis

Nervous System Disorders: coma

Psychiatric Disorders: delirium, disorientation

Renal and Genitourinary Disorders: interstitial nephritis, erectile dysfunction

Respiratory, Thoracic and Mediastinal Disorders: interstitial pneumonia

Skin and Subcutaneous Tissue Disorders: severe dermatologic reactions including bullous and other drug eruptions of the skin, cutaneous lupus erythematosus, erythema multiforme

7 DRUG INTERACTIONS

Table 2 includes drugs with clinically important drug interactions and interaction with diagnostics when administered concomitantly with ACIPHEX delayed-release tablets and instructions for preventing or managing them.

Consult the labeling of concomitantly used drugs to obtain further information about interactions with PPIs.

Table 2: Clinically Relevant Interactions Affecting Drugs Co-Administered with ACIPHEX Delayed-Release Tablets and Interactions with Diagnostics
Antiretrovirals
Clinical Impact: | The effect of PPI on antiretroviral drugs is variable. The clinical importance and the mechanisms behind these interactions are not always known.; - Decreased exposure of some antiretroviral drugs (e.g., rilpivirine, atazanavir, and nelfinavir) when used concomitantly with rabeprazole may reduce antiviral effect and promote the development of drug resistance. - Increased exposure of other antiretroviral drugs (e.g., saquinavir) when used concomitantly with rabeprazole may increase toxicity. - There are other antiretroviral drugs which do not result in clinically relevant interactions with rabeprazole.
Intervention: | Rilpivirine-containing products: Concomitant use with ACIPHEX delayed-release tablets is contraindicated [see Contraindications (4)]. See prescribing information. Atazanavir: See prescribing information for atazanavir for dosing information. Nelfinavir: Avoid concomitant use with ACIPHEX delayed-release tablets. See prescribing information for nelfinavir. Saquinavir: See the prescribing information for saquinavir and monitor for potential saquinavir toxicities. Other antiretrovirals: See prescribing information.
Warfarin
Clinical Impact: | Increased INR and prothrombin time in patients receiving PPIs, including rabeprazole, and warfarin concomitantly. Increases in INR and prothrombin time may lead to abnormal bleeding and even death [see Warnings and Precautions (5.2)].
Intervention: | Monitor INR and prothrombin time. Dose adjustment of warfarin may be needed to maintain target INR range. See prescribing information for warfarin.
Methotrexate
Clinical Impact: | Concomitant use of rabeprazole with methotrexate (primarily at high dose) may elevate and prolong serum levels of methotrexate and/or its metabolite hydroxymethotrexate, possibly leading to methotrexate toxicities. No formal drug interaction studies of methotrexate with PPIs have been conducted [see Warnings and Precautions (5.9)].
Intervention: | A temporary withdrawal of ACIPHEX delayed-release tablets may be considered in some patients receiving high dose methotrexate administration.
Digoxin
Clinical Impact: | Potential for increased exposure of digoxin [see Clinical Pharmacology (12.3)].
Intervention: | Monitor digoxin concentrations. Dose adjustment of digoxin may be needed to maintain therapeutic drug concentrations. See prescribing information for digoxin.
Drugs Dependent on Gastric pH for Absorption (e.g., iron salts, erlotinib, dasatinib, nilotinib, mycophenolate mofetil, ketoconazole, itraconazole)
Clinical Impact: | Rabeprazole can reduce the absorption of other drugs due to its effect on reducing intragastric acidity.
Intervention: | Mycophenolate mofetil (MMF): Co-administration of PPIs in healthy subjects and in transplant patients receiving MMF has been reported to reduce the exposure to the active metabolite, mycophenolic acid (MPA), possibly due to a decrease in MMF solubility at an increased gastric pH. The clinical relevance of reduced MPA exposure on organ rejection has not been established in transplant patients receiving ACIPHEX delayed-release tablets and MMF. Use ACIPHEX delayed-release tablets with caution in transplant patients receiving MMF. See the prescribing information for other drugs dependent on gastric pH for absorption.
Combination Therapy with Clarithromycin and Amoxicillin
Clinical Impact: | Concomitant administration of clarithromycin with other drugs can lead to serious adverse reactions, including potentially fatal arrhythmias, and are contraindicated. Amoxicillin also has drug interactions.
Intervention: | See Contraindications and Warnings and Precautions in prescribing information for clarithromycin. See Drug Interactions in prescribing information for amoxicillin.
Tacrolimus
Clinical Impact: | Potentially increased exposure of tacrolimus, especially in transplant patients who are intermediate or poor metabolizers of CYP2C19.
Intervention: | Monitor tacrolimus whole blood trough concentrations. Dose adjustment of tacrolimus may be needed to maintain therapeutic drug concentrations. See prescribing information for tacrolimus.
Interactions with Investigations of Neuroendocrine Tumors
Clinical Impact: | Serum chromogranin A (CgA) levels increase secondary to PPI-induced decreases in gastric acidity. The increased CgA level may cause false positive results in diagnostic investigations for neuroendocrine tumors.
Intervention: | Temporarily stop ACIPHEX delayed-release tablets treatment at least 14 days before assessing CgA levels and consider repeating the test if initial CgA levels are high. If serial tests are performed (e.g. for monitoring), the same commercial laboratory should be used for testing, as reference ranges between tests may vary.
Interaction with Secretin Stimulation Test
Clinical Impact: | Hyper-response in gastrin secretion in response to secretin stimulation test, falsely suggesting gastrinoma.
Intervention: | Temporarily stop treatment with ACIPHEX delayed-release tablets at least 14 days before assessing to allow gastrin levels to return to baseline.
False Positive Urine Tests for THC
Clinical Impact: | There have been reports of false positive urine screening tests for tetrahydrocannabinol (THC) in patients receiving PPIs.
Intervention: | An alternative confirmatory method should be considered to verify positive results.

8 USE IN SPECIFIC POPULATIONS

8.1 Pregnancy

Risk Summary

There are no available human data on ACIPHEX use in pregnant women to inform the drug associated risk. The background risk of major birth defects and miscarriage for the indicated populations are unknown. However, the background risk in the U.S. general population of major birth defects is 2 to 4% and of miscarriage is 15 to 20% of clinically recognized pregnancies. No evidence of adverse developmental effects were seen in animal reproduction studies with rabeprazole administered during organogenesis at 13 and 8 times the human area under the plasma concentration-time curve (AUC) at the recommended dose for GERD, in rats and rabbits, respectively [see Data].

Changes in bone morphology were observed in offspring of rats treated with oral doses of a different PPI through most of pregnancy and lactation. When maternal administration was confined to gestation only, there were no effects on bone physeal morphology in the offspring at any age [see Data].

Data

Animal Data

Embryo-fetal developmental studies have been performed in rats during organogenesis at intravenous doses of rabeprazole up to 50 mg/kg/day (plasma AUC of 11.8 µg∙hr/mL, about 13 times the human exposure at the recommended oral dose for GERD) and rabbits at intravenous doses up to 30 mg/kg/day (plasma AUC of 7.3 µg∙hr/mL, about 8 times the human exposure at the recommended oral dose for GERD) and have revealed no evidence of harm to the fetus due to rabeprazole.

Administration of rabeprazole to rats in late gestation and during lactation at an oral dose of 400 mg/kg/day (about 195-times the human oral dose based on mg/m^2) resulted in decreases in body weight gain of the pups.

A pre- and postnatal developmental toxicity study in rats with additional endpoints to evaluate bone development was performed with a different PPI at about 3.4 to 57 times an oral human dose on a body surface area basis. Decreased femur length, width and thickness of cortical bone, decreased thickness of the tibial growth plate, and minimal to mild bone marrow hypocellularity were noted at doses of this PPI equal to or greater than 3.4 times an oral human dose on a body surface area basis. Physeal dysplasia in the femur was also observed in offspring after in utero and lactational exposure to the PPI at doses equal to or greater than 33.6 times an oral human dose on a body surface area basis. Effects on maternal bone were observed in pregnant and lactating rats in a pre- and postnatal toxicity study when the PPI was administered at oral doses of 3.4 to 57 times an oral human dose on a body surface area basis. When rats were dosed from gestational day 7 through weaning on postnatal day 21, a statistically significant decrease in maternal femur weight of up to 14% (as compared to placebo treatment) was observed at doses equal to or greater than 33.6 times an oral human dose on a body surface area basis.

A follow-up developmental toxicity study in rats with further time points to evaluate pup bone development from postnatal day 2 to adulthood was performed with a different PPI at oral doses of 280 mg/kg/day (about 68 times an oral human dose on a body surface area basis) where drug administration was from either gestational day 7 or gestational day 16 until parturition. When maternal administration was confined to gestation only, there were no effects on bone physeal morphology in the offspring at any age.

8.2 Lactation

Risk Summary

Lactation studies have not been conducted to assess the presence of rabeprazole in human milk, the effects of rabeprazole on the breastfed infant, or the effects of rabeprazole on milk production. Rabeprazole is present in rat milk. The development and health benefits of breastfeeding should be considered along with the mother's clinical need for ACIPHEX and any potential adverse effects on the breastfed infant from ACIPHEX or from the underlying maternal condition.

8.4 Pediatric Use

The safety and effectiveness of ACIPHEX delayed-release tablets have been established in pediatric patients for adolescent patients 12 years of age and older for the treatment of symptomatic GERD. Use of ACIPHEX delayed-release tablets in this age group is supported by adequate and well controlled studies in adults and a multicenter, randomized, open-label, parallel-group study in 111 adolescent patients 12 to 16 years of age. Patients had a clinical diagnosis of symptomatic GERD, or suspected or endoscopically proven GERD and were randomized to either 10 mg or 20 mg once daily for up to 8 weeks for the evaluation of safety and efficacy. The adverse reaction profile in adolescent patients was similar to that of adults. The related reported adverse reactions that occurred in ≥2% of patients were headache (5%) and nausea (2%). There were no adverse reactions reported in these studies that were not previously observed in adults.

The safety and effectiveness of ACIPHEX delayed-release tablets have not been established in pediatric patients for:

- Healing of Erosive or Ulcerative GERD
- Maintenance of Healing of Erosive or Ulcerative GERD
- Treatment of Symptomatic GERD
- Healing of Duodenal Ulcers
- Helicobacter pylori Eradication to Reduce the Risk of Duodenal Ulcer Recurrence
- Treatment of Pathological Hypersecretory Conditions, Including Zollinger-Ellison Syndrome

ACIPHEX delayed-release 20 mg tablets are not recommended for use in pediatric patients less than 12 years of age because the tablet strength exceeds the recommended dose for these patients [see Dosage and Administration (2)]. For pediatric patients 1 year to less than 12 years of age consider another rabeprazole formulation. The safety and effectiveness of a different dosage form and dosage strength of rabeprazole has been established in pediatric patients 1 to 11 years for the treatment of GERD.

Juvenile Animal Data

Studies in juvenile and young adult rats and dogs were performed. In juvenile animal studies rabeprazole sodium was administered orally to rats for up to 5 weeks and to dogs for up to 13 weeks, each commencing on Day 7 post-partum and followed by a 13-week recovery period. Rats were dosed at 5, 25, or 150 mg/kg/day and dogs were dosed at 3, 10, or 30 mg/kg/day. The data from these studies were comparable to those reported for young adult animals. Pharmacologically mediated changes, including increased serum gastrin levels and stomach changes, were observed at all dose levels in both rats and dogs. These observations were reversible over the 13-week recovery periods. Although body weights and/or crown-rump lengths were minimally decreased during dosing, no effects on the development parameters were noted in either juvenile rats or dogs.

When juvenile animals were treated for 28 days with a different PPI at doses equal to or greater than 34 times the daily oral human dose on a body surface area basis, overall growth was affected and treatment-related decreases in body weight (approximately 14%) and body weight gain, and decreases in femur weight and femur length were observed.

8.5 Geriatric Use

Of the total number of subjects (n=2009) in clinical studies of ACIPHEX delayed-release tablets, 19% were 65 years and over, while 4% were 75 years and over. No overall differences in safety or effectiveness were observed between these subjects and younger subjects, and other reported clinical experience has not identified differences in responses between the elderly and younger patients, but greater sensitivity of some older individuals cannot be ruled out.

8.6 Hepatic Impairment

Administration of ACIPHEX delayed-release tablets to patients with mild to moderate hepatic impairment (Child-Pugh Class A and B, respectively) resulted in increased exposure and decreased elimination [see Clinical Pharmacology (12.3)]. No dosage adjustment is necessary in patients with mild to moderate hepatic impairment. There is no information in patients with severe hepatic impairment (Child-Pugh Class C). Avoid use of ACIPHEX delayed-release tablets in patients with severe hepatic impairment; however, if treatment is necessary, monitor patients for adverse reactions [see Warnings and Precautions (5), Adverse Reactions (6)].

10 OVERDOSAGE

Seven reports of accidental overdosage with rabeprazole have been received. The maximum reported overdose was 80 mg. There were no clinical signs or symptoms associated with any reported overdose. Patients with Zollinger-Ellison syndrome have been treated with up to 120 mg rabeprazole once daily. No specific antidote for rabeprazole is known. Rabeprazole is extensively protein bound and is not readily dialyzable.

In the event of overdosage, treatment should be symptomatic and supportive.

If over-exposure occurs, call your Poison Control Center at 1-800-222-1222 for current information on the management of poisoning or overdosage.

11 DESCRIPTION

The active ingredient in ACIPHEX delayed-release tablets is rabeprazole sodium, which is a proton pump inhibitor. It is a substituted benzimidazole known chemically as 2-[[[4-(3-methoxypropoxy)-3-methyl-2-pyridinyl]-methyl]sulfinyl]-1H– benzimidazole sodium salt. It has an empirical formula of C18H20N3NaO3S and a molecular weight of 381.42. Rabeprazole sodium is a white to slightly yellowish-white solid. It is very soluble in water and methanol, freely soluble in ethanol, chloroform, and ethyl acetate and insoluble in ether and n-hexane. The stability of rabeprazole sodium is a function of pH; it is rapidly degraded in acid media, and is more stable under alkaline conditions. The structural figure is:

Figure 1

ACIPHEX is available for oral administration as delayed-release, enteric-coated tablets containing 20 mg of rabeprazole sodium.

Inactive ingredients of the 20 mg tablet are carnauba wax, crospovidone, diacetylated monoglycerides, ethylcellulose, hydroxypropyl cellulose, hypromellose phthalate, magnesium stearate, mannitol, sodium hydroxide, sodium stearyl fumarate, talc, and titanium dioxide. Iron oxide yellow is the coloring agent for the tablet coating. Iron oxide red is the ink pigment.

12 CLINICAL PHARMACOLOGY

12.1 Mechanism of Action

Rabeprazole belongs to a class of antisecretory compounds (substituted benzimidazole proton-pump inhibitors) that do not exhibit anticholinergic or histamine H2-receptor antagonist properties, but suppress gastric acid secretion by inhibiting the gastric H^+, K^+ATPase at the secretory surface of the gastric parietal cell. Because this enzyme is regarded as the acid (proton) pump within the parietal cell, rabeprazole has been characterized as a gastric proton-pump inhibitor. Rabeprazole blocks the final step of gastric acid secretion.

In gastric parietal cells, rabeprazole is protonated, accumulates, and is transformed to an active sulfenamide. When studied in vitro, rabeprazole is chemically activated at pH 1.2 with a half-life of 78 seconds. It inhibits acid transport in porcine gastric vesicles with a half-life of 90 seconds.

12.2 Pharmacodynamics

Antisecretory Activity

The antisecretory effect begins within one hour after oral administration of 20 mg ACIPHEX delayed-release tablets. The median inhibitory effect of rabeprazole on 24 hour gastric acidity is 88% of maximal after the first dose. A 20 mg dose of ACIPHEX delayed-release tablets inhibits basal and peptone meal-stimulated acid secretion versus placebo by 86% and 95%, respectively, and increases the percent of a 24-hour period that the gastric pH>3 from 10% to 65% (see table below). This relatively prolonged pharmacodynamic action compared to the short pharmacokinetic half-life (1 to 2 hours) reflects the sustained inactivation of the H^+, K^+ATPase.

Table 3: Gastric Acid Parameters: ACIPHEX Delayed-Release Tablets versus Placebo After 7 Days of Once Daily Dosing
Parameter | ACIPHEX delayed-release tablets (20 mg once daily) | Placebo
Basal Acid Output (mmol/hr) | 0.4 [(p<0.01 versus placebo)] | 2.8
Stimulated Acid Output (mmol/hr) | 0.6 | 13.3
% Time Gastric pH>3 | 65 | 10

Compared to placebo, 10 mg, 20 mg, and 40 mg of ACIPHEX delayed-release tablets, administered once daily for 7 days significantly decreased intragastric acidity with all doses for each of four meal-related intervals and the 24-hour time period overall. In this study, there were no statistically significant differences between doses; however, there was a significant dose-related decrease in intragastric acidity. The ability of rabeprazole to cause a dose-related decrease in mean intragastric acidity is illustrated below.

Table 4: AUC Acidity (Mmol∙Hr/L): ACIPHEX Delayed-Release Tablets versus Placebo on Day 7 of Once Daily Dosing (Mean±SD)
 | ACIPHEX delayed-release tablets |  |  | Placebo (N=24)
AUC interval (hrs) | 10 mg (N=24) | 20 mg (N=24) | 40 mg (N=24) | Placebo (N=24)
08:00 – 13:00 | 19.6±21.5 [(p<0.001 versus placebo)] | 12.9±23 | 7.6±14.7 | 91.1±39.7
13:00 – 19:00 | 5.6±9.7 | 8.3±29.8 | 1.3±5.2 | 95.5±48.7
19:00 – 22:00 | 0.1±0.1 | 0.1±0.06 | 0.0±0.02 | 11.9±12.5
22:00 – 08:00 | 129.2±84 | 109.6±67.2 | 76.9±58.4 | 479.9±165
AUC 0-24 hours | 155.5±90.6 | 130.9±81 | 85.8±64.3 | 678.5±216

After administration of 20 mg ACIPHEX delayed-release tablets once daily for eight days, the mean percent of time that gastric pH greater than 3 or gastric pH greater than 4 after a single dose (Day 1) and multiple doses (Day 8) was significantly greater than placebo (see table below). The decrease in gastric acidity and the increase in gastric pH observed with 20 mg ACIPHEX delayed-release tablets administered once daily for eight days were compared to the same parameters for placebo, as illustrated below:

Table 5: Gastric Acid Parameters ACIPHEX Delayed-Release Tablets Once Daily Dosing versus Placebo on Day 1 and Day 8
 | ACIPHEX delayed-release tablets 20 mg once daily |  | Placebo
Parameter | Day 1 | Day 8 | Day 1 | Day 8
Mean AUC0-24 Acidity | 340.8 [(p<0.001 versus placebo)] | 176.9 | 925.5 | 862.4
Median trough pH (23-hr) [No inferential statistics conducted for this parameter.] | 3.77 | 3.51 | 1.27 | 1.38
% Time Gastric pH greater than 3 [Gastric pH was measured every hour over a 24-hour period.] | 54.6 | 68.7 | 19.1 | 21.7
% Time Gastric pH greater than 4 | 44.1 | 60.3 | 7.6 | 11.0

Effects on Esophageal Acid Exposure

In patients with GERD and moderate to severe esophageal acid exposure, a dose of 20 mg and 40 mg per day of ACIPHEX delayed-release tablets decreased 24-hour esophageal acid exposure. After seven days of treatment, the percentage of time that the esophageal pH was less than 4 decreased from baselines of 24.7% for 20 mg and 23.7% for 40 mg, to 5.1% and 2.0%, respectively. Normalization of 24-hour intraesophageal acid exposure was correlated to gastric pH greater than 4 for at least 35% of the 24-hour period; this level was achieved in 90% of subjects receiving ACIPHEX 20 mg and in 100% of subjects receiving ACIPHEX 40 mg. With ACIPHEX 20 mg and 40 mg per day, significant effects on gastric and esophageal pH were noted after one day of treatment, and more pronounced after seven days of treatment.

Effects on Serum Gastrin

The median fasting gastrin level increased in a dose-related manner in patients treated once daily with ACIPHEX delayed-release tablets for up to eight weeks for ulcerative or erosive esophagitis and in patients treated for up to 52 weeks to prevent recurrence of disease. The group median values stayed within the normal range.

In a group of subjects treated with 20 mg ACIPHEX delayed-release tablets for 4 weeks a doubling of mean serum gastrin concentrations was observed. Approximately 35% of these treated subjects developed serum gastrin concentrations above the upper limit of normal.

Effects on Enterochromaffin-like (ECL) Cells

Increased serum gastrin secondary to antisecretory agents stimulates proliferation of gastric ECL cells which, over time, may result in ECL cell hyperplasia in rats and mice and gastric carcinoids in rats, especially in females [see Nonclinical Toxicology (13.1)].

In over 400 patients treated with ACIPHEX delayed-release tablets (10 or 20 mg) once daily for up to one year, the incidence of ECL cell hyperplasia increased with time and dose, which is consistent with the pharmacological action of the proton pump inhibitor. No patient developed the adenomatoid, dysplastic or neoplastic changes of ECL cells in the gastric mucosa. No patient developed the carcinoid tumors observed in rats.

Endocrine Effects

Studies in humans for up to one year have not revealed clinically significant effects on the endocrine system. In healthy male subjects treated with ACIPHEX delayed-release tablets for 13 days, no clinically relevant changes have been detected in the following endocrine parameters examined: 17 β-estradiol, thyroid stimulating hormone, tri-iodothyronine, thyroxine, thyroxine-binding protein, parathyroid hormone, insulin, glucagon, renin, aldosterone, follicle-stimulating hormone, luteotrophic hormone, prolactin, somatotrophic hormone, dehydroepiandrosterone, cortisol-binding globulin, and urinary 6β-hydroxycortisol, serum testosterone and circadian cortisol profile.

Other Effects

In humans treated with ACIPHEX delayed-release tablets for up to one year, no systemic effects have been observed on the central nervous, lymphoid, hematopoietic, renal, hepatic, cardiovascular, or respiratory systems. No data are available on long-term treatment with ACIPHEX delayed-release tablets and ocular effects.

12.3 Pharmacokinetics

After oral administration of 20 mg ACIPHEX delayed-release tablets, peak plasma concentrations (Cmax) of rabeprazole occur over a range of 2 to 5 hours (Tmax). The rabeprazole Cmax and AUC are linear over an oral dose range of 10 mg to 40 mg. There is no appreciable accumulation when doses of 10 mg to 40 mg are administered every 24 hours; the pharmacokinetics of rabeprazole is not altered by multiple dosing.

Absorption

Absolute bioavailability for a 20 mg oral tablet of rabeprazole (compared to intravenous administration) is approximately 52%. When ACIPHEX delayed-release tablets are administered with a high fat meal, Tmax is variable; which concomitant food intake may delay the absorption up to 4 hours or longer. However, the Cmax and the extent of rabeprazole absorption (AUC) are not significantly altered. Thus ACIPHEX delayed-release tablets may be taken without regard to timing of meals.

Distribution

Rabeprazole is 96.3% bound to human plasma proteins.

Elimination

Metabolism: Rabeprazole is extensively metabolized. A significant portion of rabeprazole is metabolized via systemic nonenzymatic reduction to a thioether compound. Rabeprazole is also metabolized to sulphone and desmethyl compounds via cytochrome P450 in the liver. The thioether and sulphone are the primary metabolites measured in human plasma. These metabolites were not observed to have significant antisecretory activity. In vitro studies have demonstrated that rabeprazole is metabolized in the liver primarily by cytochromes P450 3A (CYP3A) to a sulphone metabolite and cytochrome P450 2C19 (CYP2C19) to desmethyl rabeprazole. CYP2C19 exhibits a known genetic polymorphism due to its deficiency in some sub-populations (e.g., 3 to 5% of Caucasians and 17 to 20% of Asians). Rabeprazole metabolism is slow in these sub-populations, therefore, they are referred to as poor metabolizers of the drug.

Excretion: Following a single 20 mg oral dose of ^14C-labeled rabeprazole, approximately 90% of the drug was eliminated in the urine, primarily as thioether carboxylic acid; its glucuronide, and mercapturic acid metabolites. The remainder of the dose was recovered in the feces. Total recovery of radioactivity was 99.8%. No unchanged rabeprazole was recovered in the urine or feces.

Specific Populations

Geriatric Patients: In 20 healthy elderly subjects administered 20 mg ACIPHEX delayed-release tablets once daily for seven days, AUC values approximately doubled and the Cmax increased by 60% compared to values in a parallel younger control group. There was no evidence of drug accumulation after once daily administration [see Use in Specific Population (8.5)].

Pediatric Patients: The pharmacokinetics of rabeprazole was studied in 12 adolescent patients with GERD 12 to 16 years of age, in a multicenter study. Patients received 20 mg ACIPHEX delayed-release tablets once daily for five or seven days. An approximate 40% increase in rabeprazole exposure was noted following 5 to 7 days of dosing compared with the exposure after 1 day dosing. Pharmacokinetic parameters in adolescent patients with GERD 12 to 16 years of age were within the range observed in healthy adult subjects.

Male and Female Patients and Racial or Ethnic Groups: In analyses adjusted for body mass and height, rabeprazole pharmacokinetics showed no clinically significant differences between male and female subjects. In studies that used different formulations of rabeprazole, AUC0-∞ values for healthy Japanese men were approximately 50 to 60% greater than values derived from pooled data from healthy men in the United States.

Patients with Renal Impairment: In 10 patients with stable end-stage renal disease requiring maintenance hemodialysis (creatinine clearance ≤5 mL/min/1.73 m^2), no clinically significant differences were observed in the pharmacokinetics of rabeprazole after a single 20 mg dose of ACIPHEX delayed-release tablets when compared to 10 healthy subjects.

Patients with Hepatic Impairment: In a single dose study of 10 patients with mild to moderate hepatic impairment (Child-Pugh Class A and B, respectively) who were administered a single 20 mg dose of ACIPHEX delayed-release tablets, AUC0-24 was approximately doubled, the elimination half-life was 2- to 3-fold higher, and total body clearance was decreased to less than half compared to values in healthy men.

In a multiple dose study of 12 patients with mild to moderate hepatic impairment administered 20 mg ACIPHEX delayed-release tablets once daily for eight days, AUC0-∞ and Cmax values increased approximately 20% compared to values in healthy age- and gender-matched subjects. These increases were not statistically significant.

No information exists on rabeprazole disposition in patients with severe hepatic impairment (Child-Pugh Class C) [see Use in Specific Populations (8.6)].

Drug Interaction Studies

Combined Administration with Antimicrobials: Sixteen healthy subjects genotyped as extensive metabolizers with respect to CYP2C19 were given 20 mg ACIPHEX delayed-release tablets, 1000 mg amoxicillin, 500 mg clarithromycin, or all 3 drugs in a four-way crossover study. Each of the four regimens was administered twice daily for 6 days. The AUC and Cmax for clarithromycin and amoxicillin were not different following combined administration compared to values following single administration. However, the rabeprazole AUC and Cmax increased by 11% and 34%, respectively, following combined administration. The AUC and Cmax for 14-hydroxyclarithromycin (active metabolite of clarithromycin) also increased by 42% and 46%, respectively. This increase in exposure to rabeprazole and 14-hydroxyclarithromycin is not expected to produce safety concerns.

Effects of Other Drugs on Rabeprazole

Antacids: Co-administration of ACIPHEX delayed-release tablets and antacids produced no clinically relevant changes in plasma rabeprazole concentrations.

Effects of Rabeprazole on Other Drugs

Studies in healthy subjects have shown that rabeprazole does not have clinically significant interactions with other drugs metabolized by the CYP450 system, such as theophylline (CYP1A2) given as single oral doses, diazepam (CYP2C9 and CYP3A4) as a single intravenous dose, and phenytoin (CYP2C9 and CYP2C19) given as a single intravenous dose (with supplemental oral dosing). Steady state interactions of rabeprazole and other drugs metabolized by this enzyme system have not been studied in patients.

Clopidogrel: Clopidogrel is metabolized to its active metabolite in part by CYP2C19. A study of healthy subjects including CYP2C19 extensive and intermediate metabolizers receiving once daily administration of clopidogrel 75 mg concomitantly with placebo or with 20 mg ACIPHEX delayed-release tablets (n=36), for 7 days was conducted. The mean AUC of the active metabolite of clopidogrel was reduced by approximately 12% (mean AUC ratio was 88%, with 90% CI of 81.7 to 95.5%) when ACIPHEX delayed-release tablets were coadministered compared to administration of clopidogrel with placebo [see Drug Interactions (7)].

Digoxin:In healthy adult subjects (n=16), co-administration of 20 mg rabeprazole sodium delayed-release tablets with 2.5 mg once daily doses of digoxin at steady state resulted in approximately 29% and 19% increase in mean Cmax and AUC(0-24) of digoxin [see Drug Interactions (7)].

Ketoconazole:In healthy adult subjects (n=19), co-administration of 20 mg rabeprazole sodium delayed-release tablets at steady state with a single 400 mg oral dose ketoconazole resulted in approximately an average of 31% reduction in both Cmax and AUC(0-inf) of ketoconazole [see Drug Interactions (7)].

Cyclosporine:In vitro incubations employing human liver microsomes indicated that rabeprazole inhibited cyclosporine metabolism with an IC50 of 62 micromolar, a concentration that is over 50 times higher than the Cmax in healthy volunteers following 14 days of dosing with 20 mg of ACIPHEX delayed-release tablets. This degree of inhibition is similar to that by omeprazole at equivalent concentrations.

12.4 Microbiology

The following in vitro data are available but the clinical significance is unknown.

Rabeprazole sodium, amoxicillin and clarithromycin as a three drug regimen has been shown to be active against most strains of Helicobacter pylori in vitro and in clinical infections [see Indications and Usage (1), Clinical Studies (14.5)].

Helicobacter pylori

Susceptibility testing of H. pylori isolates was performed for amoxicillin and clarithromycin using agar dilution methodology^1, and minimum inhibitory concentrations (MICs) were determined.

Standardized susceptibility test procedures require the use of laboratory control microorganisms to control the technical aspects of the laboratory procedures.

Incidence of Antibiotic-Resistant Organisms Among Clinical Isolates

Pretreatment Resistance: Clarithromycin pretreatment resistance rate (MIC ≥1 mcg/mL) to H. pylori was 9% (51/560) at baseline in all treatment groups combined. Greater than 99% (558/560) of patients had H. pylori isolates which were considered to be susceptible (MIC ≤0.25 mcg/mL) to amoxicillin at baseline. Two patients had baseline H. pylori isolates with an amoxicillin MIC of 0.5 mcg/mL.

For susceptibility testing information about Helicobacter pylori, see Microbiology section in prescribing information for clarithromycin and amoxicillin.

Table 6: Clarithromycin Susceptibility Test Results and Clinical/Bacteriologic Outcomes [Includes only patients with pretreatment and post-treatment clarithromycin susceptibility test results.] for a Three Drug Regimen (ACIPHEX Delayed-Release Tablets 20 mg Twice Daily, Amoxicillin 1000 mg Twice Daily, and Clarithromycin 500 mg Twice Daily for 7 or 10 Days)
Days of RAC Therapy | Clarithromycin Pretreatment Results | Total Number | H. pylori Negative (Eradicated) | H. pylori Positive (Persistent) Post-Treatment Susceptibility Results
Days of RAC Therapy | Clarithromycin Pretreatment Results | Total Number | H. pylori Negative (Eradicated) | S [Susceptible (S) MIC≤0.25 mcg/mL, Intermediate (I) MIC = 0.5 mcg/mL, Resistant (R) MIC≥1 mcg/mL] | I | R | No MIC
7 | Susceptible | 129 | 103 | 2 | 0 | 1 | 23
7 | Intermediate | 0 | 0 | 0 | 0 | 0 | 0
7 | Resistant | 16 | 5 | 2 | 1 | 4 | 4
10 | Susceptible | 133 | 111 | 3 | 1 | 2 | 16
10 | Intermediate | 0 | 0 | 0 | 0 | 0 | 0
10 | Resistant | 9 | 1 | 0 | 0 | 5 | 3

Patients with persistent H. pylori infection following rabeprazole, amoxicillin, and clarithromycin therapy will likely have clarithromycin resistant clinical isolates. Therefore, clarithromycin susceptibility testing should be done when possible. If resistance to clarithromycin is demonstrated or susceptibility testing is not possible, alternative antimicrobial therapy should be instituted.

Amoxicillin Susceptibility Test Results and Clinical/Bacteriological Outcomes: In the U.S. multicenter study, greater than 99% (558/560) of patients had H. pylori isolates which were considered to be susceptible (MIC≤0.25 mcg/mL) to amoxicillin at baseline. The other 2 patients had baseline H. pylori isolates with an amoxicillin MIC of 0.5 mcg/mL, and both isolates were clarithromycin-resistant at baseline; in one case the H. pylori was eradicated. In the 7- and 10-day treatment groups 75% (107/145) and 79% (112/142), respectively, of the patients who had pretreatment amoxicillin susceptible MICs (≤0.25 mcg/mL) were eradicated of H. pylori. No patients developed amoxicillin-resistant H. pylori during therapy.

12.5 Pharmacogenomics

In a clinical study in evaluating ACIPHEX delayed-release tablets in Japanese adult patients categorized by CYP2C19 genotype (n=6 per genotype category), gastric acid suppression was higher in poor metabolizers as compared to extensive metabolizers. This could be due to higher rabeprazole plasma levels in poor metabolizers. The clinical relevance of this is not known. Whether or not interactions of rabeprazole sodium with other drugs metabolized by CYP2C19 would be different between extensive metabolizers and poor metabolizers has not been studied.

13 NONCLINICAL TOXICOLOGY

13.1 Carcinogenesis, Mutagenesis, Impairment of Fertility

In an 88/104-week carcinogenicity study in CD-1 mice, rabeprazole at oral doses up to 100 mg/kg/day did not produce any increased tumor occurrence. The highest tested dose produced a systemic exposure to rabeprazole (AUC) of 1.40 µg∙hr/mL which is 1.6 times the human exposure (plasma AUC0-∞ = 0.88 µg∙hr/mL) at the recommended dose for GERD (20 mg/day). In a 28-week carcinogenicity study in p53+/- transgenic mice, rabeprazole at oral doses of 20, 60, and 200 mg/kg/day did not cause an increase in the incidence rates of tumors but produced gastric mucosal hyperplasia at all doses. The systemic exposure to rabeprazole at 200 mg/kg/day is about 17 to 24 times the human exposure at the recommended dose for GERD. In a 104-week carcinogenicity study in Sprague-Dawley rats, males were treated with oral doses of 5, 15, 30 and 60 mg/kg/day and females with 5, 15, 30, 60, and 120 mg/kg/day. Rabeprazole produced gastric enterochromaffin-like (ECL) cell hyperplasia in male and female rats and ECL cell carcinoid tumors in female rats at all doses including the lowest tested dose. The lowest dose (5 mg/kg/day) produced a systemic exposure to rabeprazole (AUC) of about 0.1 µg∙hr/mL which is about 0.1 times the human exposure at the recommended dose for GERD. In male rats, no treatment related tumors were observed at doses up to 60 mg/kg/day producing a rabeprazole plasma exposure (AUC) of about 0.2 µg∙hr/mL (0.2 times the human exposure at the recommended dose for GERD).

Rabeprazole was positive in the Ames test, the Chinese hamster ovary cell (CHO/HGPRT) forward gene mutation test, and the mouse lymphoma cell (L5178Y/TK+/–) forward gene mutation test. Its demethylated-metabolite was also positive in the Ames test. Rabeprazole was negative in the in vitro Chinese hamster lung cell chromosome aberration test, the in vivo mouse micronucleus test, and the in vivo and ex vivo rat hepatocyte unscheduled DNA synthesis (UDS) tests.

Rabeprazole at intravenous doses up to 30 mg/kg/day (plasma AUC of 8.8 µg∙hr/mL, about 10 times the human exposure at the recommended dose for GERD) was found to have no effect on fertility and reproductive performance of male and female rats.

14 CLINICAL STUDIES

14.1 Healing of Erosive or Ulcerative GERD in Adults

In a U.S., multicenter, randomized, double-blind, placebo-controlled study, 103 patients were treated for up to eight weeks with placebo, 10 mg, 20 mg, or 40 mg ACIPHEX delayed-release tablets once daily. For this and all studies of GERD healing, only patients with GERD symptoms and at least grade 2 esophagitis (modified Hetzel-Dent grading scale) were eligible for entry. Endoscopic healing was defined as grade 0 or 1. Each rabeprazole dose was significantly superior to placebo in producing endoscopic healing after four and eight weeks of treatment. The percentage of patients demonstrating endoscopic healing was as follows:

Table 7: Healing of Erosive or Ulcerative Gastroesophageal Reflux Disease (GERD) Percentage of Patients Healed
 | ACIPHEX delayed-release tablets
Week | 10 mg once daily N=27 | 20 mg once daily N=25 | 40 mg once daily N=26 | Placebo N=25
4 | 63% [(p<0.001 versus placebo)] | 56% | 54% | 0%
8 | 93% | 84% | 85% | 12%

In addition, there was a statistically significant difference in favor of the ACIPHEX 10 mg, 20 mg, and 40 mg doses compared to placebo at Weeks 4 and 8 regarding complete resolution of GERD heartburn frequency (p≤0.026). All ACIPHEX groups reported significantly greater rates of complete resolution of GERD daytime heartburn severity compared to placebo at Weeks 4 and 8 (p≤0.036). Mean reductions from baseline in daily antacid dose were statistically significant for all ACIPHEX groups when compared to placebo at both Weeks 4 and 8 (p≤0.007).

In a North American multicenter, randomized, double-blind, active-controlled study of 336 patients, the percentage of patients healed at endoscopy after four and eight weeks of treatment was statistically superior in the patients treated with ACIPHEX delayed-release tablets compared to ranitidine:

Table 8: Healing of Erosive or Ulcerative Gastroesophageal Reflux Disease (GERD) Percentage of Patients Healed
Week | 20 mg ACIPHEX delayed-release tablets once daily N=167 | Ranitidine 150 mg four times daily N=169
4 | 59% [(p<0.001 versus ranitidine)] | 36%
8 | 87% | 66%

A dose of 20 mg once daily of ACIPHEX delayed-release tablets was significantly more effective than ranitidine 150 mg four times daily in the percentage of patients with complete resolution of heartburn at Weeks 4 and 8 (p<0.001). ACIPHEX was also more effective in complete resolution of daytime heartburn (p≤0.025), and nighttime heartburn (p≤0.012) at both Weeks 4 and 8, with significant differences by the end of the first week of the study.

The recommended dosage of ACIPHEX delayed-release tablets is 20 mg once daily for 4 to 8 weeks.

14.2 Long-Term Maintenance of Healing of Erosive or Ulcerative GERD in Adults

The long-term maintenance of healing in patients with erosive or ulcerative GERD previously healed with gastric antisecretory therapy was assessed in two U.S., multicenter, randomized, double-blind, placebo-controlled studies of identical design of 52 weeks duration. The two studies randomized 209 and 285 patients, respectively, to receive either 10 mg or 20 mg of ACIPHEX delayed-release tablets once daily or placebo. As demonstrated in Tables 10 and 11 below, patients treated with ACIPHEX delayed-release tablets were significantly superior to placebo in both studies with respect to the maintenance of healing of GERD and the proportions of patients remaining free of heartburn symptoms at 52 weeks. The recommended dosage of ACIPHEX delayed-release tablets is 20 mg once daily.

Table 9: Percent of Patients in Endoscopic Remission
 | ACIPHEX delayed-release tablets |  | Placebo
 | 10 mg once daily | 20 mg once daily | Placebo
Study 1 | N=66 | N=67 | N=70
Week 4 | 83% [(p<0.001 versus placebo)] | 96% | 44%
Week 13 | 79% | 93% | 39%
Week 26 | 77% | 93% | 31%
Week 39 | 76% | 91% | 30%
Week 52 | 73% | 90% | 29%
Study 2 | N=93 | N=93 | N=99
Week 4 | 89% | 94% | 40%
Week 13 | 86% | 91% | 33%
Week 26 | 85% | 89% | 30%
Week 39 | 84% | 88% | 29%
Week 52 | 77% | 86% | 29%
COMBINED STUDIES | N=159 | N=160 | N=169
Week 4 | 87% | 94% | 42%
Week 13 | 83% | 92% | 36%
Week 26 | 82% | 91% | 31%
Week 39 | 81% | 89% | 30%
Week 52 | 75% | 87% | 29%

Table 10: Percent of Patients Without Relapse in Heartburn Frequency and Daytime and Nighttime Heartburn Severity at Week 52
 | ACIPHEX delayed-release tablets |  | Placebo
 | 10 mg once daily | 20 mg once daily | Placebo
Heartburn Frequency
Study 1 | 46/55 (84%) [p≤0.001 versus placebo] | 48/52 (92%) | 17/45 (38%)
Study 2 | 50/72 (69%) | 57/72 (79%) | 22/79 (28%)
Daytime Heartburn Severity
Study 1 | 61/64 (95%) | 60/62 (97%) | 42/61 (69%)
Study 2 | 73/84 (87%) [0.001<p<0.05 versus placebo] | 82/87 (94%) | 67/90 (74%)
Nighttime Heartburn Severity
Study 1 | 57/61 (93%) | 60/61 (98%) | 37/56 (66%)
Study 2 | 67/80 (84%) | 79/87 (91%) | 64/87 (74%)

14.3 Treatment of Symptomatic GERD in Adults

Two U.S., multicenter, double-blind, placebo controlled studies were conducted in 316 adult patients with daytime and nighttime heartburn. Patients reported 5 or more periods of moderate to very severe heartburn during the placebo treatment phase the week prior to randomization. Patients were confirmed by endoscopy to have no esophageal erosions.

The percentage of heartburn free daytime and/or nighttime periods was greater with 20 mg ACIPHEX delayed-release tablets compared to placebo over the 4 weeks of study in Study RAB-USA-2 (47% vs. 23%) and Study RAB-USA-3 (52% vs. 28%). The mean decreases from baseline in average daytime and nighttime heartburn scores were significantly greater for ACIPHEX 20 mg as compared to placebo at week 4. Graphical displays depicting the daily mean daytime and nighttime scores are provided in Figures 2 to 5.

Figure 2: Mean Daytime Heartburn Scores RAB-USA-2

Figure 3: Mean Nighttime Heartburn Scores RAB-USA-2

Figure 4: Mean Daytime Heartburn Scores RAB-USA-3

Figure 5: Mean Nighttime Heartburn Scores RAB-USA-3

In addition, the combined analysis of these two studies showed 20 mg of ACIPHEX delayed-release tablets significantly improved other GERD-associated symptoms (regurgitation, belching, and early satiety) by week 4 compared with placebo (all p values <0.005).

A dose of 20 mg ACIPHEX delayed-release tablets also significantly reduced daily antacid consumption versus placebo over 4 weeks (p<0.001).

The recommended dosage of ACIPHEX delayed-release tablets is 20 mg once daily for 4 weeks.

14.4 Healing of Duodenal Ulcers in Adults

In a U.S., randomized, double-blind, multicenter study assessing the effectiveness of 20 mg and 40 mg of ACIPHEX delayed-release tablets once daily versus placebo for healing endoscopically defined duodenal ulcers, 100 patients were treated for up to four weeks. ACIPHEX was significantly superior to placebo in producing healing of duodenal ulcers. The percentages of patients with endoscopic healing are presented below:

Table 11: Healing of Duodenal Ulcers Percentage of Patients Healed
Week | ACIPHEX delayed-release tablets |  | Placebo N=33
Week | 20 mg once daily N=34 | 40 mg once daily N=33
2 | 44% | 42% | 21%
4 | 79% [p≤0.001 versus placebo] | 91% | 39%

At Weeks 2 and 4, significantly more patients in the ACIPHEX 20 and 40 mg groups reported complete resolution of ulcer pain frequency (p≤0.018), daytime pain severity (p≤0.023), and nighttime pain severity (p≤0.035) compared with placebo patients. The only exception was the 40 mg group versus placebo at Week 2 for duodenal ulcer pain frequency (p=0.094). Significant differences in resolution of daytime and nighttime pain were noted in both ACIPHEX groups relative to placebo by the end of the first week of the study. Significant reductions in daily antacid use were also noted in both ACIPHEX groups compared to placebo at Weeks 2 and 4 (p<0.001).

An international randomized, double-blind, active-controlled trial was conducted in 205 patients comparing 20 mg ACIPHEX delayed-release tablets once daily with 20 mg omeprazole once daily. The study was designed to provide at least 80% power to exclude a difference of at least 10% between ACIPHEX and omeprazole, assuming four-week healing response rates of 93% for both groups. In patients with endoscopically defined duodenal ulcers treated for up to four weeks, ACIPHEX was comparable to omeprazole in producing healing of duodenal ulcers. The percentages of patients with endoscopic healing at two and four weeks are presented below:

Table 12: Healing of Duodenal Ulcers Percentage of Patients Healed
Week | ACIPHEX delayed-release tablets 20 mg once daily N=102 | Omeprazole 20 mg once daily N=103 | 95% Confidence Interval for the Treatment Difference (ACIPHEX - Omeprazole)
2 | 69% | 61% | (–6%, 22%)
4 | 98% | 93% | (–3%, 15%)

ACIPHEX and omeprazole were comparable in providing complete resolution of symptoms.

The recommended dosage of ACIPHEX delayed-release tablets is 20 mg once daily for 4 weeks.

14.5 Helicobacter pylori Eradication in Patients with Peptic Ulcer Disease or Symptomatic Non-Ulcer Disease in Adults

The U.S. multicenter study was a double-blind, parallel-group comparison of ACIPHEX delayed-release tablets, amoxicillin, and clarithromycin for 3, 7, or 10 days vs. omeprazole, amoxicillin, and clarithromycin for 10 days. Therapy consisted of rabeprazole 20 mg twice daily, amoxicillin 1000 mg twice daily, and clarithromycin 500 mg twice daily (RAC) or omeprazole 20 mg twice daily, amoxicillin 1000 mg twice daily, and clarithromycin 500 mg twice daily (OAC). Patients with H. pylori infection were stratified in a 1:1 ratio for those with peptic ulcer disease (active or a history of ulcer in the past five years) [PUD] and those who were symptomatic but without peptic ulcer disease [NPUD], as determined by upper gastrointestinal endoscopy. The overall H. pylori eradication rates, defined as negative ^13C-UBT for H. pylori ≥6 weeks from the end of the treatment are shown in the following table. The eradication rates in the 7-day and 10-day RAC regimens were found to be similar to 10-day OAC regimen using either the Intent-to-Treat (ITT) or Per-Protocol (PP) populations. Eradication rates in the RAC 3-day regimen were inferior to the other regimens.

Table 13: Helicobacter pylori Eradication at ≥6 Weeks After the End of Treatment
 | Treatment Group Percent (%) of Patients Cured (Number of Patients) |  | Difference (RAC – OAC) [95% Confidence Interval]
 | 7-day RAC [The 95% confidence intervals for the difference in eradication rates for 7-day RAC minus 10-day RAC are (- 9.3, 6.0) in the PP population and (-9.0, 7.5) in the ITT population.] | 10-day OAC
Per Protocol [Patients were included in the analysis if they had H. pylori infection documented at baseline, defined as a positive ^13C-UBT plus rapid urease test or culture and were not protocol violators. Patients who dropped out of the study due to an adverse event related to the study drug were included in the evaluable analysis as failures of therapy.] | 84.3% (N=166) | 81.6% (N=179) | 2.8 [- 5.2, 10.7]
Intent-to-Treat [Patients were included in the analysis if they had documented H. pylori infection at baseline as defined above and took at least one dose of study medication. All dropouts were included as failures of therapy.] | 77.3% (N=194) | 73.3% (N=206) | 4.0 [- 4.4, 12.5]
 | 10-day RAC | 10-day OAC
Per Protocol | 86.0% (N=171) | 81.6% (N=179) | 4.4 [- 3.3, 12.1]
Intent-to-Treat | 78.1% (N=196) | 73.3% (N=206) | 4.8 [- 3.6, 13.2]
 | 3-day RAC | 10-day OAC
Per Protocol | 29.9% (N=167) | 81.6% (N=179) | - 51.6 [- 60.6, - 42.6]
Intent-to-Treat | 27.3% (N=187) | 73.3% (N=206) | - 46.0 [- 54.8, - 37.2]

The recommended dosage of ACIPHEX delayed-release tablets is 20 mg twice daily with amoxicillin and clarithromycin for 7 days.

14.6 Pathological Hypersecretory Conditions, Including Zollinger-Ellison Syndrome in Adults

Twelve patients with idiopathic gastric hypersecretion or Zollinger-Ellison syndrome have been treated successfully with ACIPHEX delayed-release tablets at doses from 20 to 120 mg for up to 12 months. ACIPHEX produced satisfactory inhibition of gastric acid secretion in all patients and complete resolution of signs and symptoms of acid-peptic disease where present. ACIPHEX also prevented recurrence of gastric hypersecretion and manifestations of acid-peptic disease in all patients. The high doses of ACIPHEX used to treat this small cohort of patients with gastric hypersecretion were well tolerated.

The recommended starting dosage of ACIPHEX delayed-release tablets is 60 mg once daily.

15 REFERENCES

1. Clinical and Laboratory Standards Institute (CLSI). Methods for Dilution Antimicrobial Susceptibility Tests for Bacteria That Grow Aerobically; Approved Standard—Tenth Edition. CLSI Document M07-A10, Clinical and Laboratory Standards Institute, 950 West Valley Road, Suite 2500, Wayne, Pennsylvania, 19087, USA 2015.

16 HOW SUPPLIED/STORAGE AND HANDLING

ACIPHEX 20 mg is supplied as delayed-release light yellow enteric-coated tablets. The name and strength, in mg, (ACIPHEX 20) is imprinted on one side.

Bottles of 30 (NDC 80725-243-30)

STORAGE AND HANDLING

Store at 25°C (77°F); excursions permitted to 15-30°C (59-86°F) [see USP Controlled Room Temperature]. Protect from moisture.

17 PATIENT COUNSELING INFORMATION

Advise the patient to read the FDA-approved patient labeling (Medication Guide).

Acute Tubulointerstitial Nephritis

Advise the patient or caregiver to call the patient's healthcare provider immediately if they experience signs and/or symptoms associated with -acute tubulointerstitial nephritis [see Warnings and Precautions (5.3)].

Clostridium difficile-Associated Diarrhea

Advise the patient or caregiver to immediately call the patient's healthcare provider if they experience diarrhea that does not improve [see Warnings and Precautions (5.4)].

Bone Fracture

Advise the patient or caregiver to report any fractures, especially of the hip, wrist or spine, to the patient's healthcare provider [see Warnings and Precautions (5.5)].

Severe Cutaneous Adverse Reactions

Advise the patient or caregiver to discontinue ACIPHEX and report any signs and symptoms of a severe cutaneous adverse reaction or other sign of hypersensitivity to the healthcare provider [see Warnings and Precautions (5.6)].

Cutaneous and Systemic Lupus Erythematosus

Advise the patient or caregiver to immediately call the patient's healthcare provider for any new or worsening of symptoms associated with cutaneous or systemic lupus erythematosus [see Warnings and Precautions (5.6)].

Cyanocobalamin (Vitamin B-12) Deficiency

Advise the patient or caregiver to report any clinical symptoms that may be associated with cyanocobalamin deficiency to the patient's healthcare provider if they have been receiving ACIPHEX for longer than 3 years [see Warnings and Precautions (5.7)].

Hypomagnesemia and Mineral Metabolism

Advise the patient or caregiver to report any clinical symptoms that may be associated with hypomagnesemia, hypocalcemia, hypokalemia and hyponatremia to the patient's healthcare provider, if they have been receiving ACIPHEX for at least 3 months [see Warnings and Precautions (5.8)].

Drug Interactions

Advise patients to report to their healthcare provider if they are taking rilpivirine-containing products [see Contraindications (4)], warfarin, digoxin or high-dose methotrexate [see Warnings and Precautions (5.2, 5.8, 5.9)].

Administration

- Swallow ACIPHEX delayed-release tablets whole. Do not chew, crush or split the tablets.
- For the treatment of duodenal ulcers take ACIPHEX delayed-release tablets after a meal.
- For Helicobacter pylori eradication take ACIPHEX delayed-release tablets with food.
- For all other indications ACIPHEX delayed-release tablets can be taken with or without food.
- Take a missed dose as soon as possible. If it is almost time for the next dose, skip the missed dose and go back to the normal schedule. Do not take two doses at the same time.

Distributed by Waylis Therapeutics LLC, Rahway, NJ 07065

All brand names are the trademarks of their respective owners.

MEDICATION GUIDE
ACIPHEX® (a-se-feks)
(rabeprazole sodium)
delayed-release tablets

What is the most important information I should know about ACIPHEX?
You should take ACIPHEX exactly as prescribed, at the lowest dose possible and for the shortest time needed.
ACIPHEX may help your acid-related symptoms, but you could still have serious stomach problems. Talk with your doctor.
ACIPHEX can cause serious side effects, including:

- A type of kidney problem (acute tubulointerstitial nephritis).
  Some people who take proton pump inhibitor (PPI) medicines, including ACIPHEX, may develop a kidney problem called acute tubulointerstitial nephritis that can happen at any time during treatment with ACIPHEX. Call your doctor right away if you have a decrease in the amount that you urinate or if you have blood in your urine.
- Diarrhea caused by an infection (Clostridium difficile) in your intestines. Call your doctor right away if you have watery stools or stomach pain that does not go away. You may or may not have a fever.
- Bone fractures (hip, wrist, or spine). Bone fractures in the hip, wrist, or spine may happen in people who take multiple daily doses of PPI medicines and for a long period of time (a year or longer). Tell your doctor if you have a bone fracture, especially in the hip, wrist, or spine.
- Certain types of lupus erythematosus. Lupus erythematosus is an autoimmune disorder (the body's immune cells attack other cells or organs in the body). Some people who take PPI medicines, including ACIPHEX, may develop certain types of lupus erythematosus or have worsening of the lupus they already have. Call your doctor right away if you have new or worsening joint pain or a rash on your cheeks or arms that gets worse in the sun.

Talk to your doctor about your risk of these serious side effects.
ACIPHEX can have other serious side effects. See "What are the possible side effects of ACIPHEX?"

What is ACIPHEX?
ACIPHEX is a prescription medicine called a proton pump inhibitor (PPI).
ACIPHEX reduces the amount of acid in your stomach.
In adults, ACIPHEX is used for:

- 8 weeks up to 16 weeks to heal acid-related damage to the lining of the esophagus (called erosive esophagitis or EE) and to relieve symptoms, such as heartburn pain.
- maintaining healing of the esophagus and relief of symptoms related to EE. It is not known if ACIPHEX is safe and effective if used longer than 12 months (1 year).
- up to 4 weeks to treat daytime and nighttime heartburn and other symptoms that happen with Gastroesophageal Reflux Disease (GERD).
- up to 4 weeks for the healing and relief of symptoms of duodenal ulcers.
- 7 days with certain antibiotic medicines to treat an infection and stomach (duodenal) ulcers caused by bacteria called H. pylori.
- the long-term treatment of conditions where your stomach makes too much acid. This includes a rare condition called Zollinger-Ellison syndrome.

In adolescents 12 years of age and older, ACIPHEX is used for up to 8 weeks to treat symptoms of GERD.
It is not known if ACIPHEX is safe and effective in children less than 12 years of age for other uses.
ACIPHEX delayed-release tablets should not be used in children under 12 years of age.

Do not take ACIPHEX if you are:

- allergic to rabeprazole, any other PPI medicine, or any of the ingredients in ACIPHEX. See the end of this Medication Guide for a complete list of ingredients.
- taking a medicine that contains rilpivirine (EDURANT, COMPLERA, ODEFSEY) used to treat HIV-1 (Human Immunodeficiency Virus).

Before you take ACIPHEX, tell your doctor about all of your medical conditions, including if you:

- have low magnesium levels, low calcium levels and low potassium levels in your blood.
- have liver problems.
- are pregnant or plan to become pregnant. It is not known if ACIPHEX can harm your unborn baby.
- are breastfeeding or plan to breastfeed. It is not known if ACIPHEX passes into your breast milk. Talk to your doctor about the best way to feed your baby if you take ACIPHEX.

Tell your doctor about all the medicines you take, including prescription and over-the-counter medicines, vitamins, and herbal supplements. Especially tell your doctor if you take an antibiotic that contains clarithromycin or amoxicillin or if you take warfarin (COUMADIN, JANTOVEN), methotrexate (OTREXUP, RASUVO, TREXALL, XATMEP), digoxin (LANOXIN), or a water pill (diuretic).

How should I take ACIPHEX?

- Take ACIPHEX exactly as prescribed.
- ACIPHEX is usually taken 1 time each day. Your doctor will tell you the time of day to take ACIPHEX, based on your medical condition.
- ACIPHEX can be taken with or without food. Your doctor will tell you whether to take this medicine with or without food based on your medical condition.
- Swallow each ACIPHEX tablet whole. Do not chew, crush, or split ACIPHEX tablets. Tell your doctor if you cannot swallow tablets whole.
- If you miss a dose of ACIPHEX, take it as soon as possible. If it is almost time for your next dose, you should not take the missed dose. You should take your next dose at your regular time. Do not take 2 doses at the same time.
- If you take too much ACIPHEX, call your doctor or your poison control center at 1-800-222-1222 right away, or go to the nearest emergency room.
- If your doctor prescribes antibiotic medicines with ACIPHEX, read the patient information that comes with the antibiotic medicines before you take them.

What are the possible side effects of ACIPHEX?
ACIPHEX can cause serious side effects, including:

- See "What is the most important information I should know about ACIPHEX?"
- Interaction with warfarin.Taking warfarin with a PPI medicine may lead to an increased risk of bleeding and death. If you take warfarin, your doctor may check your blood to see if you have an increased risk of bleeding. If you take warfarin during treatment with ACIPHEX, tell your doctor right away if you have any signs or symptoms of bleeding, including:

- pain, swelling or discomfort
- headaches, dizziness, or weakness
- unusual bruising (bruises that happen without known cause or that grow in size)
- nosebleeds
- bleeding gums
- bleeding from cuts take a long time to stop

- menstrual bleeding that is heavier than normal
- pink or brown urine
- red or black stools
- coughing up blood
- vomiting blood or vomit that looks like coffee grounds

- Low vitamin B-12 levels in the body can happen in people who have taken ACIPHEX for a long time (more than 3 years). Tell your doctor if you have symptoms of low vitamin B-12 levels, including shortness of breath, lightheadedness, irregular heartbeat, muscle weakness, pale skin, feeling tired, mood changes, and tingling or numbness in the arms and legs.
- Low magnesium levels in the body can happen in people who have taken ACIPHEX for at least 3 months. Tell your doctor if you have symptoms of low magnesium levels, including seizures, dizziness, irregular heartbeat, jitteriness, muscle aches or weakness, and spasms of hands, feet or voice.
- Stomach growths (fundic gland polyps). People who take PPI medicines for a long time have an increased risk of developing a certain type of stomach growths called fundic gland polyps, especially after taking PPI medicines for more than 1 year.
- Severe skin reactions. ACIPHEX can cause rare but serious skin reactions that may affect any part of your body. These serious skin reactions may need to be treated in a hospital and may be life threatening:
  - Skin rash which may have blistering, peeling or bleeding on any part of your skin (including your lips, eyes, mouth, nose, genitals, hands or feet).
  - You may also have fever, chills, body aches, shortness of breath, or enlarged lymph nodes.

Stop taking ACIPHEX and call your doctor right away. These symptoms may be the first sign of a severe skin reaction.
The most common side effects of ACIPHEX in adults include: pain, sore throat, gas, infection, and constipation.
The most common side effects of ACIPHEX in adolescents 12 years of age and older include: headache, diarrhea, nausea, vomiting, and stomach-area (abdomen) pain.
These are not all of the possible side effects of ACIPHEX. Call your doctor for medical advice about side effects. You may report side effects to FDA at 1-800-FDA-1088.

How should I store ACIPHEX?
Store ACIPHEX tablets in a dry place at room temperature between 68°F to 77°F (20°C to 25°C).
Keep ACIPHEX and all medicines out of the reach of children.

General Information about the safe and effective use of ACIPHEX.
Medicines are sometimes prescribed for purposes other than those listed in a Medication Guide. Do not use ACIPHEX for a condition for which it was not prescribed. Do not give ACIPHEX to other people, even if they have the same symptoms that you have. It may harm them.
You can ask your doctor or pharmacist for information about ACIPHEX that is written for health professionals.

What are the ingredients in ACIPHEX?
Active ingredient: rabeprazole sodium
Inactive ingredients: carnauba wax, crospovidone, diacetylated monoglycerides, ethylcellulose, hydroxypropyl cellulose, hypromellose phthalate, magnesium stearate, mannitol, sodium hydroxide, sodium stearyl fumarate, talc, and titanium dioxide. Iron oxide yellow is the coloring agent for the tablet coating. Iron oxide red is the ink pigment.
Distributed by:
Waylis Therapeutics LLC,
Rahway, NJ 07065
All brand names are the trademarks of their respective owners.
For more information, go to www.aciphex.com.

This Medication Guide has been approved by the U.S. Food and Drug Administration.

Rev 10/2025

PRINCIPAL DISPLAY PANEL - 20 mg Tablet Bottle Label

NDC 80725-243-30

Rx only

AcipHex®
rabeprazole sodium
delayed-release
tablets

20 mg

Waylis
THERAPEUTICS

30 tablets